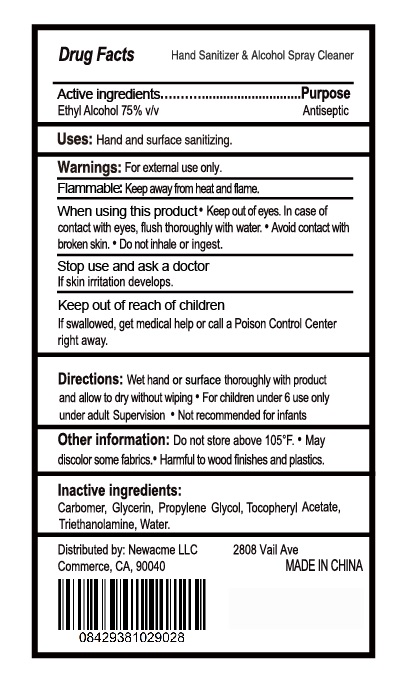 DRUG LABEL: Hand Sanitizer
NDC: 75123-001 | Form: GEL
Manufacturer: Yunnan Xicao Resource Development Company Limited
Category: otc | Type: HUMAN OTC DRUG LABEL
Date: 20200609

ACTIVE INGREDIENTS: ALCOHOL 70 mL/100 mL
INACTIVE INGREDIENTS: WATER; AMINOMETHYLPROPANOL; CARBOXYPOLYMETHYLENE

75123-001 Hand Sanitizer 75% Alcohol

Active Ingredient

Ethyl Alcohol 70%

Purpose

Antimicrobial

Use

■Helps reduce bacteria on the skin
Kills most germs and viruses
■Leaves hands feling soft

WARNINGS

For external use only
Do notuse | 1 In or near the eyes
When using this product
■Putenough product in your palm to cover hands and
rub hands together briskly unilldry.
■I Keep awayfrom fire and flame.
Do notusein or near the eyes.
1 I Use Hand Sanitizerto help reduce bacteria on the skin
that could cause disease.
Recommended for repeated use.

Keep out of reach of children
If swallowed , get medical help or contact a Poison Control Center right away

Directions

1 1 Healthcare personnel hand antisepsis: take suitable
amount of the antiseptic gel onyour palm, rubyour
hands thoroughly for 1 minute until completelydry.
■Surgical hand antisepsis: clean hands, forearms and
lower 1/3 of upper arms with antibacterial soap.Apply
and rub the antiseptic gel Hand Sanitizer gelon hands,
forearms and lower 1/3 of upper arms for 3 minutes. Air
dry. Then puton sterilegloves.

Inactive ingredients

Water (Aqua),Aminomethyl Propanol, Carbomer